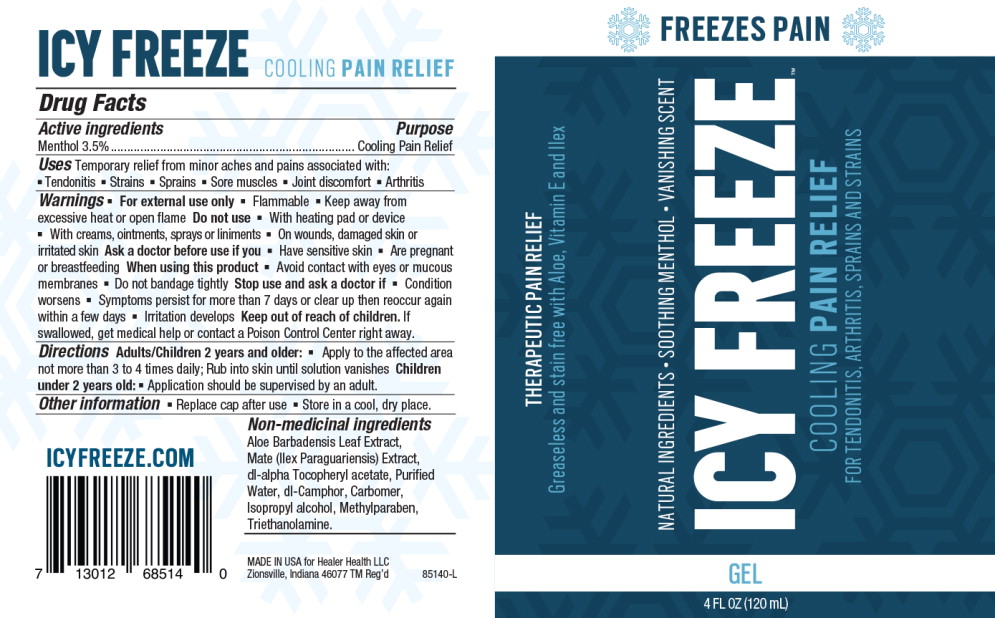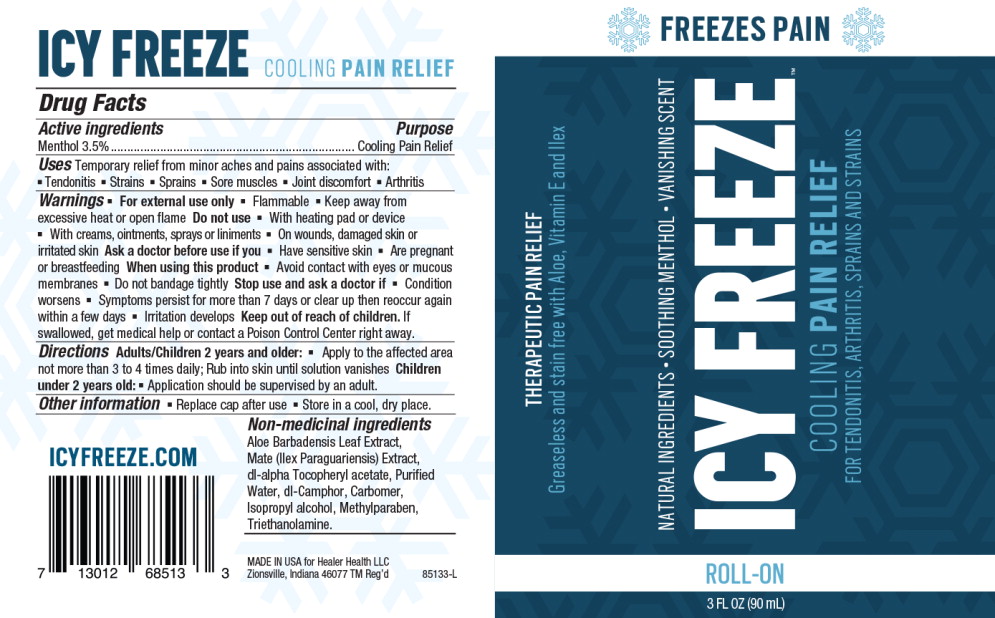 DRUG LABEL: ICY FREEZE
NDC: 66902-165 | Form: GEL
Manufacturer: NATURAL ESSENTIALS, INC.
Category: otc | Type: HUMAN OTC DRUG LABEL
Date: 20171201

ACTIVE INGREDIENTS: MENTHOL 35 mg/1 mL
INACTIVE INGREDIENTS: ALOE VERA LEAF; CAMPHOR (SYNTHETIC); CARBOMER HOMOPOLYMER TYPE C (ALLYL PENTAERYTHRITOL CROSSLINKED); ILEX PARAGUARIENSIS LEAF; ISOPROPYL ALCOHOL; METHYLPARABEN; TROLAMINE; WATER

ICY FREEZE COOLING PAIN RELIEF

Drug Facts

Active ingredient

Menthol 3.5%

Purpose

Cooling Pain Relief

Uses

Temporary relief from minor aches and pains associated with:

- Tendonitis
- Strains
- Sprains
- Sore muscles
- Joint discomfort
- Arthritis

Warnings

- For external use only
- Flammable
- Keep away from excessive heat or open flame

Do not use

- With heating pad or device
- With creams, ointments, sprays or liniments
- On wounds, damaged skin or irritated skin

Ask a doctor before use if you

- Have sensitive skin
- Are pregnant or breastfeeding

When using this product

- Avoid contact with eyes or mucous membranes
- Do not bandage tightly

Stop use and ask a doctor if

- Condition worsens
- Symptoms persist for more than 7 days or clear up then reoccur again within a few days
- Irritation develops

Keep out of reach of children. If swallowed, get medical help or contact a Poison Control Center right away.

Directions Adults/Children 2 years and older:

- Apply to the affected area not more than 3 to 4 times daily; Rub into skin until solution vanishes

Children under 2 years old:

- Application should be supervised by an adult.

Other information

- Replace cap after use
- Store in a cool, dry place.

INACTIVE INGREDIENT

Non-medicinal ingredients Aloe Barbadensis Leaf Extract, Mate (Ilex Paraguariensis) Extract, dl-alpha Tocopheryl acetate, Purified Water, dl-Camphor, Carbomer, Isopropyl alcohol, Methylparaben, Triethanolamine.

MADE IN USA for Healer Health LLC

Zionsville, Indiana 46077 TM Reg'd 85140-L

ICYFREEZE.COM

PACKAGE LABEL

Principal Display Panel - Icy Freeze 3oz Gel Pump

FREEZES PAIN

THERAPUTIC PAIN RELIEF

Greaseless and stain free with Aloe, Vitamin E and Ilex

NATURAL INGREDIENTS • SOOTHING MENTHOL • VANISHING SCENT

ICY FREEZE

COOLING PAIN RELIEF

FOR TENDONITIS, ARTHRITIS, SPRAINS AND STRAINS

GEL

4 FL OZ (120 mL)

PACKAGE LABEL

Principal Display Panel - Icy Freeze 3oz Roll On

FREEZES PAIN

THERAPUTIC PAIN RELIEF

Greaseless and stain free with Aloe, Vitamin E and Ilex

NATURAL INGREDIENTS • SOOTHING MENTHOL • VANISHING SCENT

ICY FREEZE

COOLING PAIN RELIEF

FOR TENDONITIS, ARTHRITIS, SPRAINS AND STRAINS

ROLL-ON

3 FL OZ (90 mL)